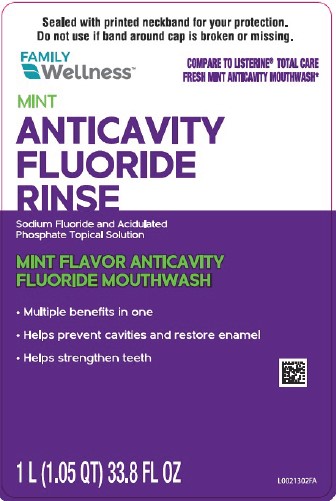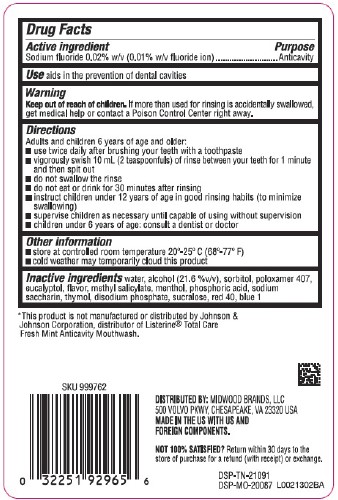 DRUG LABEL: Anticavity Fluoride Rinse
NDC: 55319-163 | Form: MOUTHWASH
Manufacturer: Family Dollar Stores, Inc
Category: otc | Type: HUMAN OTC DRUG LABEL
Date: 20260224

ACTIVE INGREDIENTS: SODIUM FLUORIDE 0.1 mg/1 mL
INACTIVE INGREDIENTS: WATER; ALCOHOL; SORBITOL; POLOXAMER 407; EUCALYPTOL; METHYL SALICYLATE; MENTHOL; PHOSPHORIC ACID; SACCHARIN SODIUM; THYMOL; SODIUM PHOSPHATE, DIBASIC, ANHYDROUS; SUCRALOSE; FD&C RED NO. 40; FD&C BLUE NO. 1

Family Wellness 163.005/163AG
Anticavity Fluoride Rinse

Active ingredient

Sodium fluoride 0.02% (0.01% w/v fluoride ion)

Purpose

Anticavity

Use

aids in the prevention of dental cavities

Warning

for this product

Keep out of reach of children.

If more than used for rinsing is accidentally swallowed, get medical help or contact a Poison Control Center right away.

Directions

Adults and children 12 years of age and older:

- use twice daily after brushing your teeth with toothpaste
- vigorously swish 10 mL (2 teaspoonfuls) of rinse between your teeth for 1 minute and then spit out
- do not swallow the rinse
- do not eat or drink for 30 minutes after rinsing
- instruct children under 12 years of age in good rinsing habits (to minimize swallowing)
- supervise children as necessary until capable of using without supervision
- children under 12 years of age: consult a dentist or doctor

Other information

- store at controlled room temperature 20⁰-25⁰ C (68⁰ - 77⁰F)
- cold weather may temporarily cloud this product

Inactive ingredients

water, alcohol (21.6 %v/v), sorbitol, poloxamer 407, eucalyptol, flavor, methyl salicylate, menthol, phosphoric acid, sodium saccharin, thymol, disodium phosphate, sucralose, red 40, blue 1

Disclaimer

*This product is not manufacturd or distributed by Johnson & Johnson Corporation, distributerof Listerine® Total Care Fresh Mint Anticavity Mouthwash.

Adverse Reaction

DISTRIBUTED BY: MIDWOOD BRANDS, LLC

500 VOLVO PKWY, CHESAPEAKE, VA 23320 USA

MADE IN THE US WITH US AND FOREIGN COMPONENTS.

NOT 100% SATISFIED? Return within 30 days to the store of purchase for a refund (with receipt) or Exchange.

DSP-TN-21091

DSP-MO-20087

principal display panel

Sealed with printed neckband for your protection.

Do not use if band around cap is broken or missing.

FAMILY WELLNESS™

COMPARE TO LISTERINE® TOTAL CARE FRESH MINT ANTICAVITY MOUTHWASH*

MINT

ANTICAVITY FLUORIDE RINSE

Sodium Fluoride and Acidulated Phosphate Topical Solution

MINT FLAVOR ANTICAVITY FLUORIDE MOUTHWASH

- Multiple benefits in one
- Helps prevent cavities and restore enamel
- Helps strengthen teeth

1 L (1.05 QT) 33.8 FL OZ